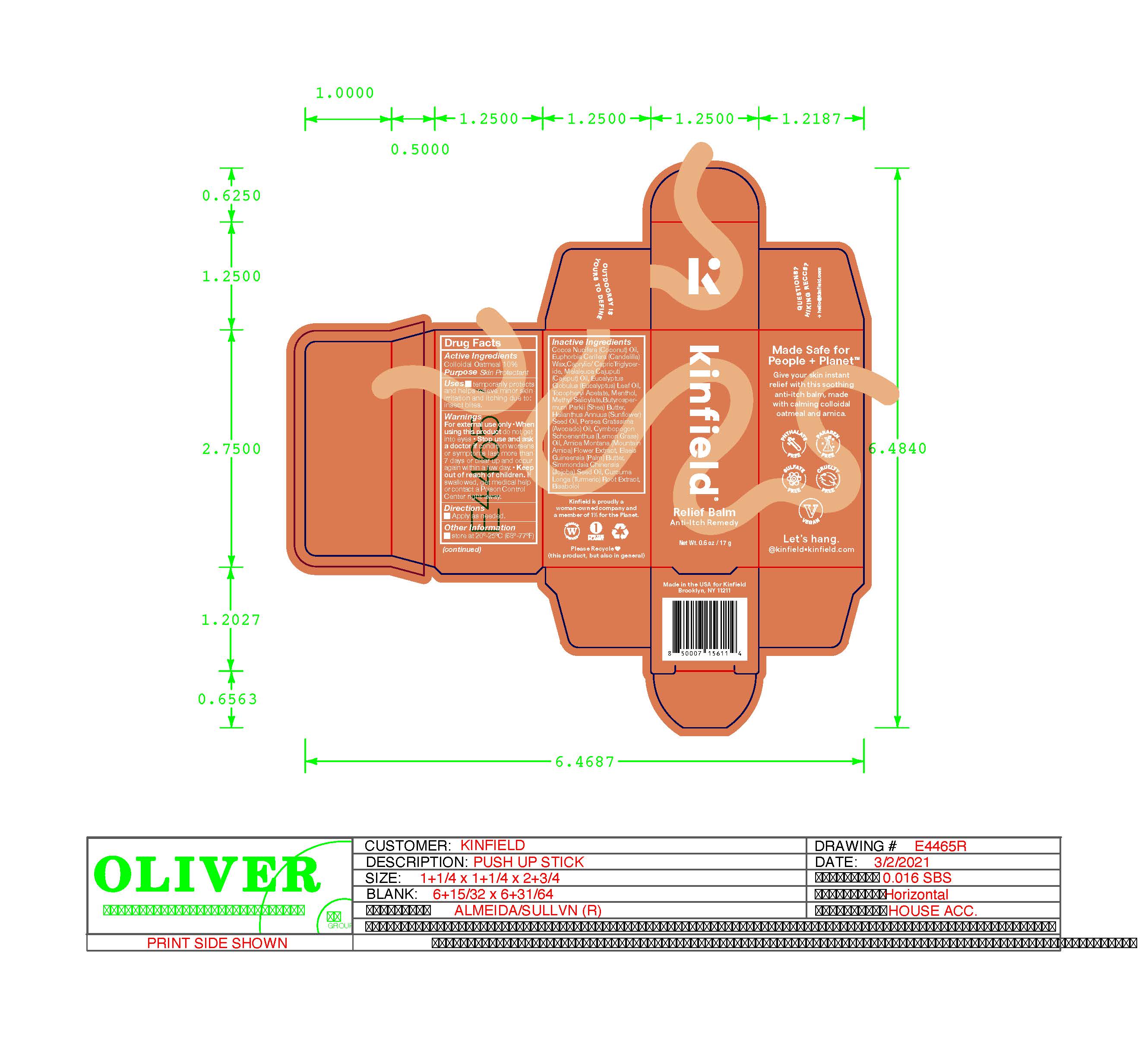 DRUG LABEL: Kinfield Relief Balm Anti-Itch Remedy
NDC: 81750-020 | Form: LOTION
Manufacturer: Kinfield, Inc.
Category: otc | Type: HUMAN OTC DRUG LABEL
Date: 20251230

ACTIVE INGREDIENTS: OATMEAL 10 g/17 g
INACTIVE INGREDIENTS: COCOS NUCIFERA WHOLE; CANDELILLA WAX; MELALEUCA CAJUPUTI WHOLE; EUCALYPTUS GLOBULUS LEAF; .ALPHA.-TOCOPHEROL ACETATE; MENTHOL; METHYL SALICYLATE; SHEA BUTTER; HELIANTHUS ANNUUS WHOLE; PERSEA AMERICANA LEAF; CYMBOPOGON SCHOENANTHUS OIL; ARNICA MONTANA FLOWER; ELAEIS GUINEENSIS WHOLE; SIMMONDSIA CHINENSIS WHOLE; CURCUMA LONGA WHOLE; .BETA.-BISABOLOL

DRUG FACTS

Purpose

Skin Protectant

Active Ingredients

Colloidal Oatmeal 10.00%

Uses

Temporarily protects and helps releive minor skin irritation and itching due to insect bites

Warnings

Fox external use only.

When using this product do not get into eyes

Stop use and ask a doctor if

- condition worsens
- symptoms last more than 7 days or clear up and occur again within a few days

Keep out of reach of children. If swalled, get medical help or contact a Poison Control Center right away.

Directions

- Apply as needed.

Inactive Ingredients

Cocos Nucifera Oil, Euphorbia Cerifera Wax, Caprylic/Capric Triglyceride, Melaleuca Cajuputi Oil, Eucalyptus Globulus Leaf Oil, Tocopheryl Acetate, Menthol, Methyl Salicylate, Butyrospermum Parkii Butter, Helianthus Annuus Seed Oil, Persea Gratissima Oil, Cymbopogon Schoenanthus Oil, Arnica Montana Flower Extract, Elaeis Guineensis Butter, Simmondsia Chinensis Seed Oil, Curcuma Longa Root Extract, Bisabolol

Other Information

Store at 20-25C (68-77)F